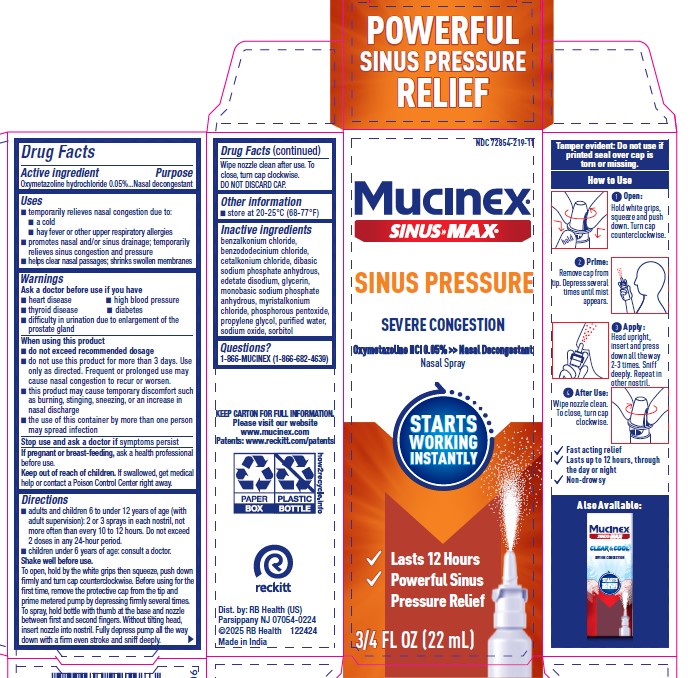 DRUG LABEL: Mucinex Sinus Max Sinus Pressure Severe Congestion
NDC: 72854-219 | Form: SPRAY
Manufacturer: RB Health (US) LLC
Category: otc | Type: HUMAN OTC DRUG LABEL
Date: 20251216

ACTIVE INGREDIENTS: OXYMETAZOLINE HYDROCHLORIDE 0.05 g/100 mL
INACTIVE INGREDIENTS: BENZALKONIUM CHLORIDE; BENZODODECINIUM CHLORIDE; PHOSPHORUS PENTOXIDE; CETALKONIUM CHLORIDE; SODIUM PHOSPHATE, DIBASIC, ANHYDROUS; GLYCERIN; MYRISTALKONIUM CHLORIDE; SODIUM OXIDE; PROPYLENE GLYCOL; SORBITOL; EDETATE DISODIUM; SODIUM PHOSPHATE, MONOBASIC, UNSPECIFIED FORM; WATER

Mucinex Sinus Max Sinus Pressure Severe Congestion

Drug Facts

Active ingredient
Oxymetazoline hydrochloride 0.05%

Purpose:

Nasal Decongestant

Uses:

■ temporarily relieves nasal congestion due to:
■ a cold
■ hay fever or other upper respiratory allergies
■ promotes nasal and/or sinus drainage; temporarily
relieves sinus congestion and pressure
■ helps clear nasal passages; shrinks swollen membranes

Purpose:

Nasal Decongestant

Warnings
Ask a doctor before use if you have
■ heart disease

■ high blood pressure
■ thyroid disease

■ diabetes
■ difficulty in urination due to enlargement of the
prostate gland

When using this product
■ do not exceed recommended dosage
■ do not use this product for more than 3 days. Use
only as directed. Frequent or prolonged use may
cause nasal congestion to recur or worsen.
■ this product may cause temporary discomfort such
as burning, stinging, sneezing, or an increase in
nasal discharge
■ the use of this container by more than one person
may spread infection

Stop use and ask a doctor if symptoms persist

Directions
■ adults and children 6 to under 12 years of age (with
adult supervision): 2 or 3 sprays in each nostril, not
more often than every 10 to 12 hours. Do not exceed
2 doses in any 24-hour period.
■ children under 6 years of age: consult a doctor.

Shake well before use.
To open, hold by the white grips then squeeze, push down
firmly and turn cap counterclockwise. Before using for the
first time, remove the protective cap from the tip and
prime metered pump by depressing firmly several times.
To spray, hold bottle with thumb at the base and nozzle
between first and second fingers.Without tilting head,
insert nozzle into nostril. Fully depress pump all the way
down with a firm even stroke and sniff deeply.
Wipe nozzle clean after use. To
close, turn cap clockwise.
DO NOT DISCARD CAP.

PREGNANCY OR BREAST FEEDING

If pregnant or breast-feeding, ask a health professional
before use.

Keep out of reach of children. If swallowed, get medical
help or contact a Poison Control Center right away.

Other information
■ store at 20-25°C (68-77°F)

Inactive ingredients
benzalkonium chloride,
benzododecinium chloride,
cetalkonium chloride, dibasic
sodium phosphate anhydrous,
edetate disodium, glycerin,
monobasic sodium phosphate
anhydrous, myristalkonium
chloride, phosphorous pentoxide,
propylene glycol, purified water,
sodium oxide, sorbitol

Questions?
1-866-MUCINEX (1-866-682-4639)

Dist. by: RB Health (US)
Parsippany NJ 07054-0224